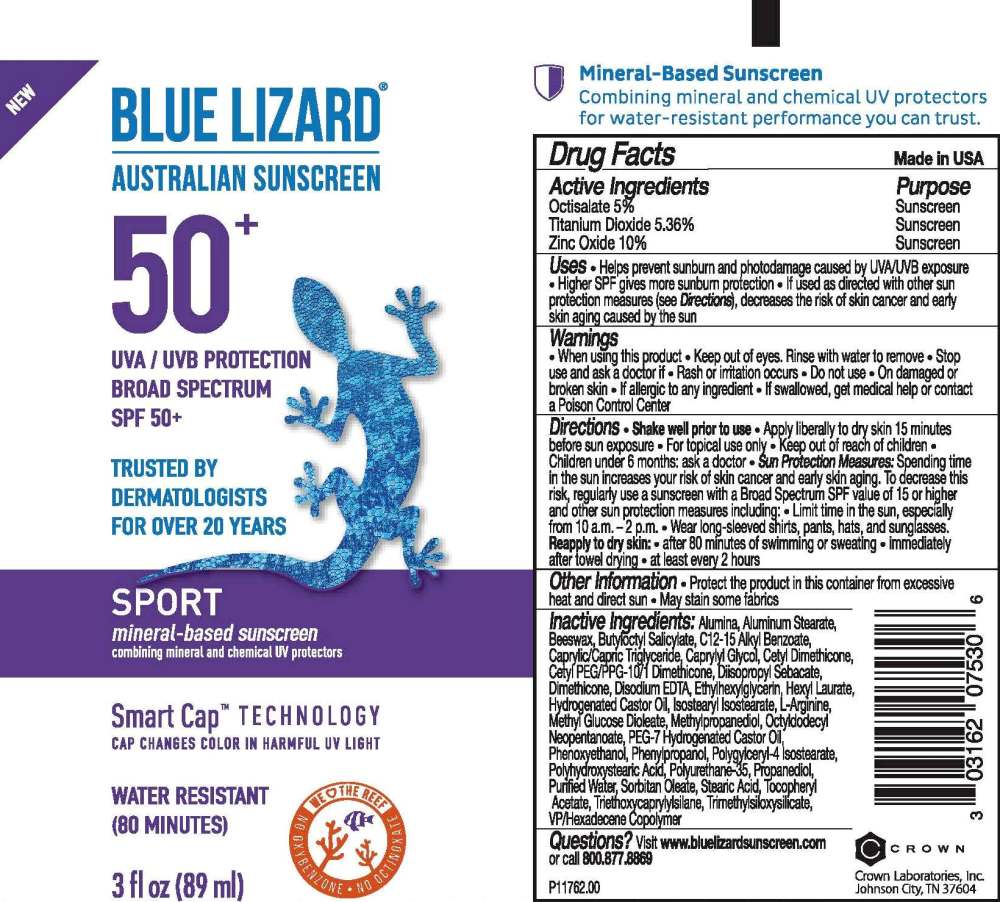 DRUG LABEL: Blue Lizard Sport SPF 50 Sunscreen
NDC: 0316-2075 | Form: LOTION
Manufacturer: Crown Laboratories
Category: otc | Type: HUMAN OTC DRUG LABEL
Date: 20260112

ACTIVE INGREDIENTS: OCTISALATE 55.5 mg/1 mL; TITANIUM DIOXIDE 59.5 mg/1 mL; ZINC OXIDE 111 mg/1 mL
INACTIVE INGREDIENTS: MEDIUM-CHAIN TRIGLYCERIDES; ALUMINUM OXIDE; ALUMINUM STEARATE; TRIETHOXYCAPRYLYLSILANE; YELLOW WAX; ARGININE; METHYLPROPANEDIOL; CETYL PEG/PPG-10/1 DIMETHICONE (HLB 5); ALKYL (C12-15) BENZOATE; EDETATE DISODIUM; CAPRYLYL GLYCOL; HEXYL LAURATE; HYDROGENATED CASTOR OIL; METHYL GLUCOSE DIOLEATE; OCTYLDODECYL NEOPENTANOATE; PEG-7 HYDROGENATED CASTOR OIL; POLYGLYCERYL-4 ISOSTEARATE; PHENOXYETHANOL; PROPANEDIOL; WATER; SORBITAN MONOOLEATE; STEARIC ACID; .ALPHA.-TOCOPHEROL ACETATE; DIMETHICONE; TRIMETHYLSILOXYSILICATE (M/Q 0.8-1.0); HEXADECYL POVIDONE (4 HEXADECYL BRANCHES/REPEAT); POLYHYDROXYSTEARIC ACID (2300 MW); CETYL DIMETHICONE 25; ETHYLHEXYLGLYCERIN; PHENYLPROPANOL; DIISOPROPYL SEBACATE; POLYURETHANE-35 (NOT MORE THAN 500 MPA.S AT 40%); BUTYLOCTYL SALICYLATE; ISOSTEARYL ISOSTEARATE

Blue Lizard Sport SPF 50 Sunscreen

Active Ingredients

Octisalate 5%

Titanium Dioxide 5.36%

Zinc Oxide 10%

Purpose

Sunscreen

Uses

- Helps prevent sunburn and photodamage caused by UVA/UVB exposure
- Higher SPF gives more sunburn protection
- If used as directed with other sun protection measures (see Directions), decreases the risks of skin cancer and early skin aging caused by the sun

Warnings

• When using this product • Keep out of eyes. Rinse with water to remove

• Stop use and ask doctor if • Rash or irritation occurs

• Do not use • On damaged or broken skin • If allergic to any ingredient

• If swallowed, get medical help or contact a Poison Control Center

Directions

• Shake well prior to use

• Apply liberally to dry skin 15 minutes before sun exposure

• For topical use only

• Children under 6 months: ask a doctor

• Sun Protection Measures: Spending time in the sun increases your risk of skin cancer and early skin aging. To decrease this risk, regularly use a sunscreen with a Broad Spectrum SPF value of 15 or higher and other sun protection measures including: Limit time in the sun, especially from 10 a.m. - 2 p.m.

• Wear long-sleeved shirts, pants, hats, and sunglasses.

• Reapply to dry skin: • after 80 minutes of swimming or sweating • immediately after towel drying • at least every 2 hours

Other Information

- Protect the product in this container from excessive heat and direct sun
- May stain some fabrics

Inactive Ingredients

Alumina, Aluminum Stearate, Beeswax, Butyloctyl Salicylate, C12-15 Alkyl Benzoate, Capylic/Capric Triglyceride, Caprylyl Glycol, Cetyl Dimethicone, Cetyl PEG/PPG-10/1 Dimethicone, Diisopropyl Sebacate, Dimethicone, Disodium EDTA, Ethylhexylglycerin, Hexyl Laurate, Hydrogenated Castor Oil, Isostearyl Isostearate, L-Arginine, Methyl Glucose Dioleate, Methylpropanediol, Octyldodecyl Neopentanoate, PEG-7 Hydrogenated Castor Oil, Phenoxyethanol, Phenylpropanol, Polyglyceryl-4 Isostearate, Polyhydroxystearic Acid, Polyurethane-35, Propanediol, Purified Water, Sorbitan Oleate, Stearic Acid, Tocopheryl Acetate, Triethoxycaprylylsilane, Trimethylsiloxysilicate, VP Hexadecene Copolymer

Questions?

Visit www.bluelizardsunscreen.com or call 800.877.8869

Crown Laboratories, Inc., Johnson City, TN 37604

RECENT MAJOR CHANGES

Formatted Uses section

Formatted Directions section

Blue Lizard Sport 3oz Tube

BLUE LIZARD

AUSTRALIAN SUNSCREEN

50+

UVA/UVB PROTECTION

BROAD SPECTRUM

SPF 50+

TRUSTED BY DERMATOLOGIST FOR OVER 20 YEARS

SPORT

mineral-based sunscreen

combining mineral and chemical UV protectors

Smart Cap TECHNOLOGY

CAP CHANGES COLOR IN HARMFUL UV LIGHT

WATER RESISTANT (80 MINUTES)

Mineral-Based Sunscreen

Combing mineral and chemical UV protectors for water-resistant perfomrance you can trust.

3fl oz (89ml)

P11762.00